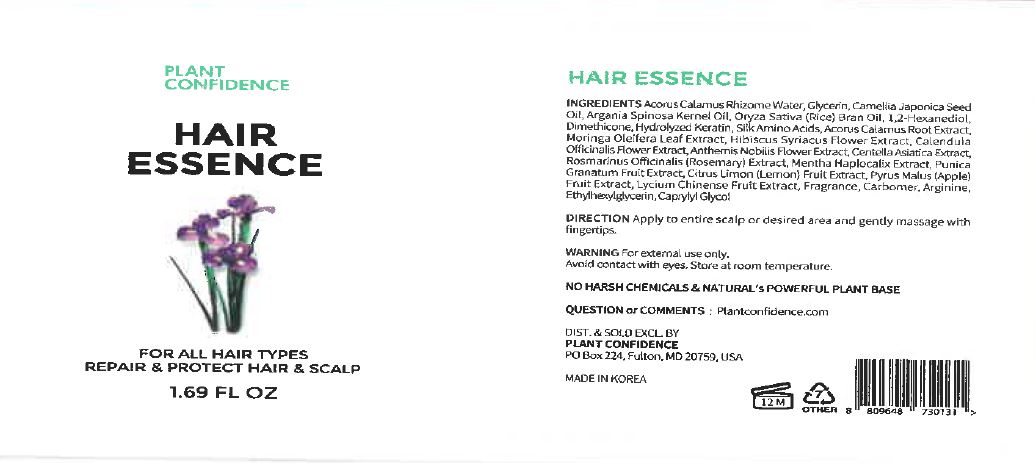 DRUG LABEL: Hair Essence
NDC: 71484-0010 | Form: LIQUID
Manufacturer: Ddoruroo Co., Ltd.
Category: otc | Type: HUMAN OTC DRUG LABEL
Date: 20200305

ACTIVE INGREDIENTS: MORINGA OLEIFERA LEAF 1 g/100 mL; CALENDULA OFFICINALIS FLOWER 1 g/100 mL
INACTIVE INGREDIENTS: WATER

Drug Facts

ACTIVE INGREDIENT

Camellia Japonica Seed Oil
Argania Spinosa Kernel Oil
Dimethicone
Oryza Sativa (Rice) Bran Oil
Silk Amino Acids
Hydrolyzed Keratin
Acorus Calamus Root Extract
Moringa Oleifera Leaf Extract
Hibiscus Syriacus Flower Extract
Calendula Officinalis Flower Extract
Anthemis Nobilis Flower Extract
Centella Asiatica Extract
Rosmarinus Officinalis (Rosemary) Extract
Mentha Haplocalix Extract
Punica Granatum Fruit Extract
Citrus Limon (Lemon) Fruit Extract
Pyrus Malus (Apple) Fruit Extract
Lycium Chinense Fruit Extract

INACTIVE INGREDIENT

Acorus Calamus Rhizome Water
Glycerin

1,2-Hexanediol

Fragrance
Carbomer
Arginine
Ethylhexylglycerin
Caprylyl glycol

PURPOSE

for all hair types, repair & protect hair & scalp

KEEP OUT OF REACH OF THE CHILDREN

INDICATIONS AND USAGE

apply to entire scalp or desired area and gently massage with fingertips

WARNINGS

1. Do not use in the following cases(Eczema and scalp wounds)
2.Side Effects
1)Due to the use of this druf if rash, irritation, itching and symptopms of hypersnesitivity occur dicontinue use and consult your phamacisr or doctor
3.General Precautions
1)If in contact with the eyes, wash out thoroughty with water If the symptoms are servere, seek medical advice immediately
2)This product is for exeternal use only. Do not use for internal use
4.Storage and handling precautions
1)If possible, avoid direct sunlight and store in cool and area of low humidity
2)In order to maintain the quality of the product and avoid misuse
3)Avoid placing the product near fire and store out in reach of children

DOSAGE AND ADMINISTRATION

for external use only